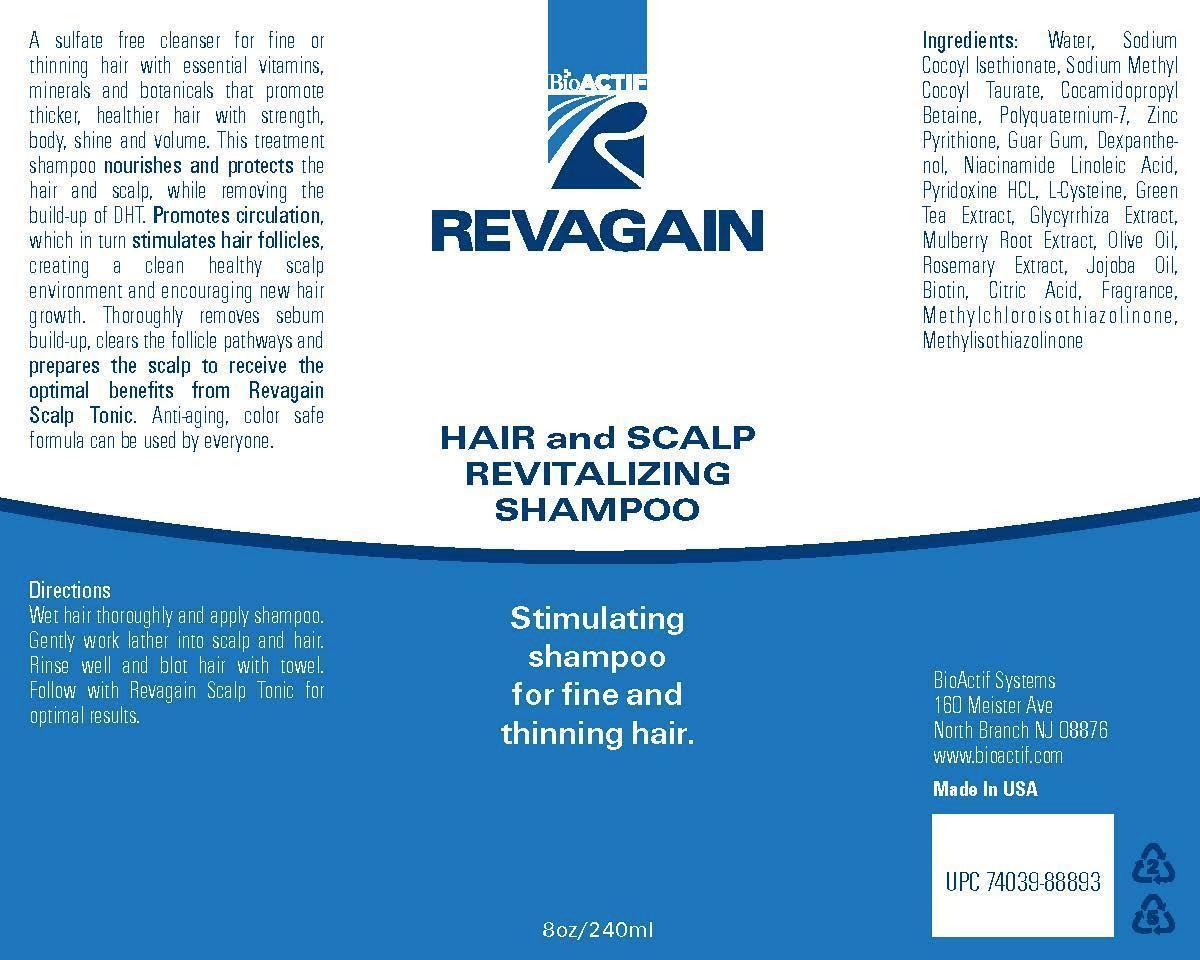 DRUG LABEL: REVAGAIN Hair and Scalp revitalizing
NDC: 69808-1001 | Form: SHAMPOO
Manufacturer: AFFINITY GROUP L.L.C.
Category: otc | Type: HUMAN OTC DRUG LABEL
Date: 20150507

ACTIVE INGREDIENTS: PYRITHIONE ZINC 2.1 g/100 mL
INACTIVE INGREDIENTS: WATER; CITRIC ACID MONOHYDRATE; NIACINAMIDE

Drug Facts

ACTIVE INGREDIENT

zinc pyrithione

INACTIVE INGREDIENT

water, guar gum, cocamidopropyl betaine, niacinamide, linoleic acid, l-cycteine, green tea ext, olive oil, jojoba oil, biotin, l-menthol

PURPOSE

hair growth and loss prevention

keep out or reach of the children

INDICATIONS AND USAGE

wet hair thoroughly and apply shampoo.
gently work lather into scalp and hair.
rinse well and blot hair with towel
follow with REVAGAIN scalp tonic for optimal results

WARNINGS

1. Do not use in the following cases(Eczema and scalp wounds)
2.Side Effects
1)Due to the use of this product if rash, irritation, itching and symptopms of hypersnesitivity occur dicontinue use and consult ypur phamacisr or doctor
3.General Precautions
1)If in contact with the eyes, wash out thoroughty with water If the symptoms are servere, seek medical advice immediately
2)This product is for exeternal use only. Do not use for internal use
4.Storage and handling precautions
1)If possible, avoid direct sunlight and store in cool and area of low humidity
2)In order to maintain the quality of the product and avoid misuse
3)Avoid placing the product near fire and store out in reach of children

DOSAGE AND ADMINISTRATION

for external use only